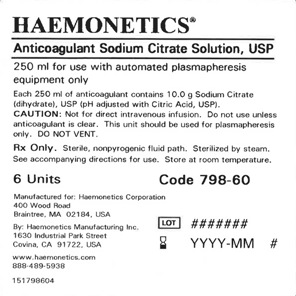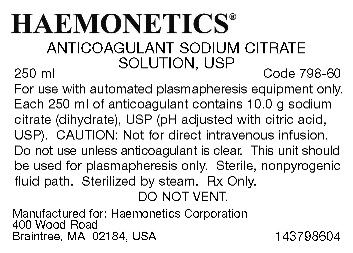 DRUG LABEL: Sodium Citrate
NDC: 53157-798 | Form: SOLUTION
Manufacturer: Haemonetics Manufacturing Inc
Category: prescription | Type: HUMAN PRESCRIPTION DRUG LABEL
Date: 20150209
DEA Schedule: CII

ACTIVE INGREDIENTS: SODIUM CITRATE 10.0 g/250 mL

Anticoagulant Sodium Citrate Solution, USP

DESCRIPTION

Re-Order Product Code: 798-60

250 mL volume. Single use container.

Sterile, nonpyrogenic fluid path. Sterilized by steam.

Store at room temperature.

INDICATIONS AND USAGE

For use with automated plasmapheresis equipment only. Use according to equipment manufacturer’s instructions. This unit should be used for plasmapheresis only.

CONTRAINDICATIONS

Not for direct intravenous infusion.

WARNINGS

Avoid excessive heat. Protect from freezing. Do NOT vent.

PRECAUTIONS

Do not use unless solution is clear and no leaks detected.

General

Rx only. Discard unused portion.

Recommended Storage: Store at room temperature (25°C / 77°F).

HOW SUPPLIED

250 mL volume bag.

Each 250 ml contains:

10.0 g sodium citrate (dihydrate), USP

PACKAGE/LABEL PRINCIPAL DISPLAY PANEL

Bag Label

Envelope Label

References

HAEMONETICS and THE Blood Management Company are trademarks of Haemonetics Corporation.

Manufactured for:

Haemonetics Corporation

400 Wood Road

Braintree, MA 02184, USA

By: Haemonetics Manufacturing Inc.

1630 Industrial Park Street

Covina, CA 91722, USA